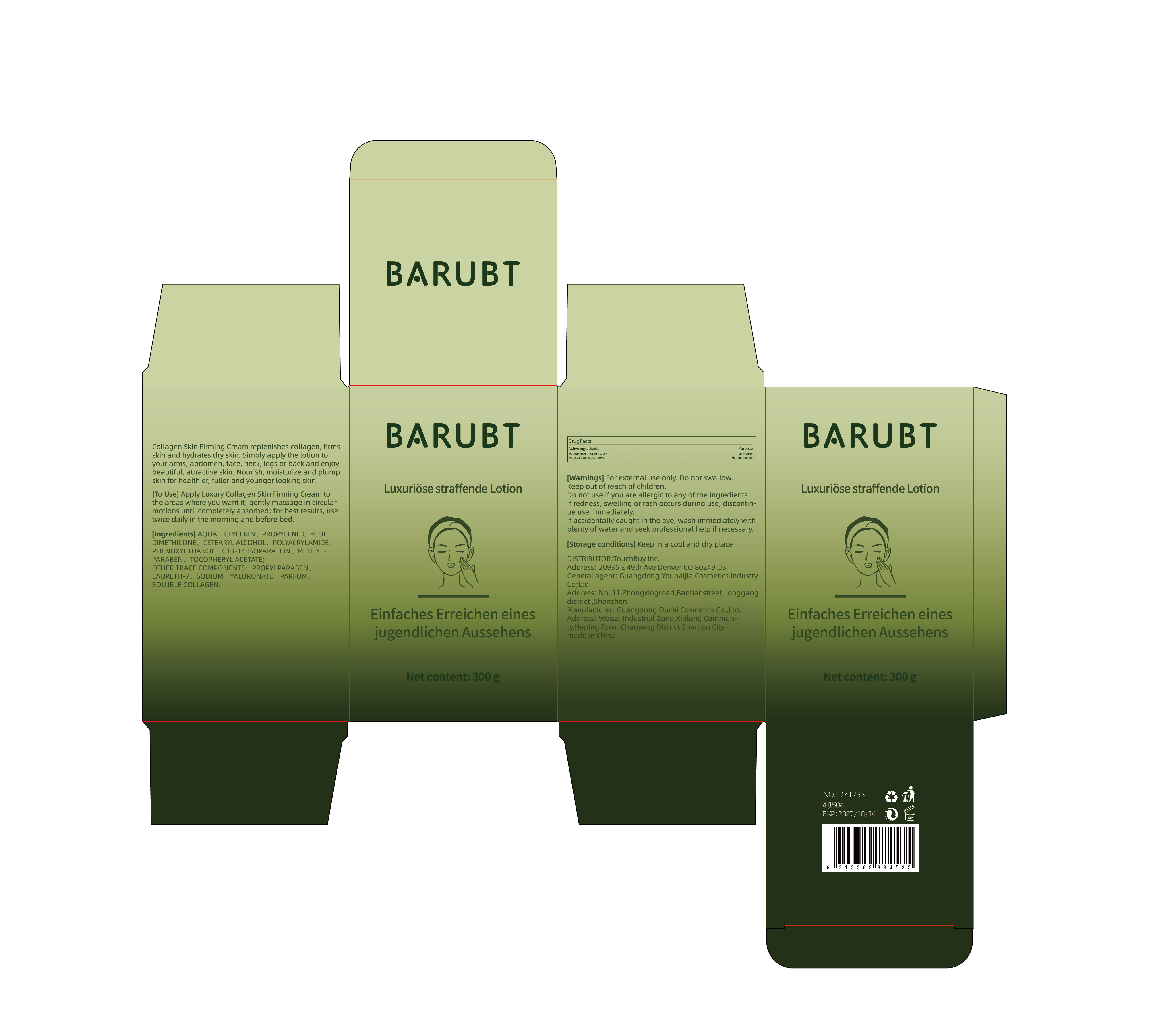 DRUG LABEL: BARUBT Luxuriose straffende lo-tion
NDC: 84712-035 | Form: LOTION
Manufacturer: Guangdong Youbaijia Cosmetic Industry Co., Ltd
Category: otc | Type: HUMAN OTC DRUG LABEL
Date: 20241127

ACTIVE INGREDIENTS: SODIUM HYALURONATE 0.15 g/300 g; MARINE COLLAGEN, SOLUBLE 0.15 g/300 g
INACTIVE INGREDIENTS: GLYCERIN 15 g/300 g

ACTIVE INGREDIENT

SODIUM HYALURONATE 0.05%
SOLUBLE COLLAGEN 0.05%

INACTIVE INGREDIENT

AQUA. GLYCERIN, PROPYLENE GLYCOL, DIMETHICONE, CETEARYL ALCOHOL, POLYACRYLAMIDE, PHENOXYETHANOL, C13-14 ISOPARAFFIN, METHYL- PARABEN, TOCOPHERYL ACETATE.PROPYLPARABEN. LAURETH-7. PARFUM

DO NOT USE

on damaged or broken skin

Keep away from children. Do not swallow.

PURPOSE

firms skin and hydrates dry skin

QUESTIONS

Contact name: Jessie Peng
Company phone number: +1 818 579 7288
Company e-mail: jessie@registeragentllc.com

STOP USE

lf skin becomes red or irritated, discontinue use immediately and wash with water.

WHEN USING

keep out of eyes. Rinse with water to remove

WARNINGS

For external use only.

INDICATIONS AND USAGE

Collagen Skin Firming Cream replenishes collagen, firms skin and hydrates dry skin.Simply apply the lotion to your arms, abdomen, face, neck, legs or back and enjoy beautiful, attractive skin.Nourish, moisturize and plump skin for healthier, fuller and younger looking skin.

DOSAGE AND ADMINISTRATION

Apply Luxury Collagen Skin Firming Cream to the areas where you want it; gently massage in circular motions until completely absorbed; for best results, use twice daily in the morning and before bed.

STORAGE AND HANDLING

Keep away from light and in a dry place.